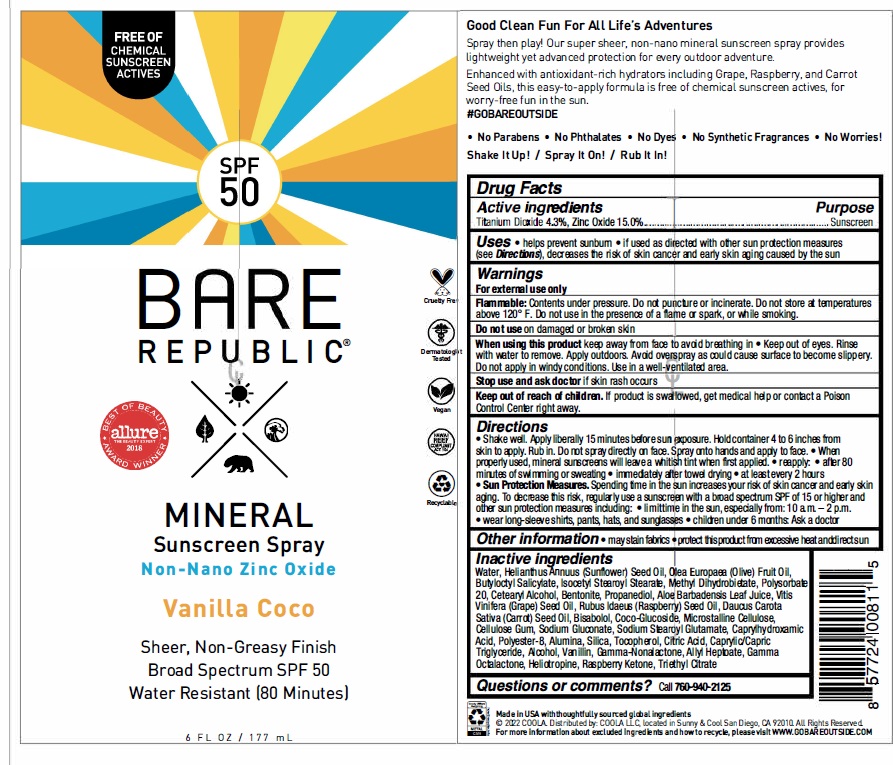 DRUG LABEL: Bare Republic SPF 50 Mineral Sunscreen Vanilla Coco
NDC: 79753-048 | Form: SPRAY
Manufacturer: COOLA, LLC
Category: otc | Type: HUMAN OTC DRUG LABEL
Date: 20240522

ACTIVE INGREDIENTS: ZINC OXIDE 15 g/100 mL; TITANIUM DIOXIDE 4.3 g/100 mL
INACTIVE INGREDIENTS: PIPERONAL; OLIVE OIL; POLYESTER-8 (1400 MW, CYANODIPHENYLPROPENOYL CAPPED); WATER; TRIETHYL CITRATE; TOCOPHEROL; PROPANEDIOL; SODIUM GLUCONATE; SODIUM STEAROYL GLUTAMATE; CAPRYLHYDROXAMIC ACID; POLYSORBATE 20; ALOE VERA LEAF; CARROT SEED OIL; SUNFLOWER OIL; CETOSTEARYL ALCOHOL; ALCOHOL; VANILLIN; .GAMMA.-OCTALACTONE; GRAPE SEED OIL; BUTYLOCTYL SALICYLATE; ISOCETYL STEAROYL STEARATE; METHYL DIHYDROABIETATE; SILICON DIOXIDE; MICROCRYSTALLINE CELLULOSE; CARBOXYMETHYLCELLULOSE SODIUM, UNSPECIFIED FORM; ALUMINUM OXIDE; CITRIC ACID MONOHYDRATE; COCO GLUCOSIDE; 4-(P-HYDROXYPHENYL)-2-BUTANONE; MEDIUM-CHAIN TRIGLYCERIDES; .GAMMA.-NONALACTONE; ALLYL HEPTANOATE; BENTONITE; RASPBERRY SEED OIL; LEVOMENOL

Bare Republic Mineral Spray SPF 50 - Vanilla Coco

ACTIVE INGREDIENT

Titanium Dioxide - 4.3%

Zinc Oxide - 15.0%

PURPOSE

Sunscreen

Uses

• Helps prevent sunburn
• If used as directed with other sun protection measures (see Directions), decreases the risk of skin cancer and early skin aging caused by the sun.

WARNINGS

- For external use only
- Flammable: Contents under pressure. Do not puncture or incinerate. Do not store at temperatures above 120° F. Do not use in the presence of a flame or spark, or while smoking.
- Do not use on damaged or broken skin
- When using this product keep away from face to avoid breathing in • Keep out of eyes. Rinse with water to remove. Apply outdoors. Avoid overspray as could cause surface to become slippery. Do not apply in windy conditions. Use in a well ventilated area.
- Stop use and ask doctor if skin rash occurs

Keep out of reach of children. If product is swallowed, get medical help or contact a Poison Control Center right away.

Directions

• Shake well. Apply liberally 15 minutes before sun exposure. Hold container 4 to 6 inches from skin to apply. Rub in. Do not spray directly on face. Spray onto hands and apply to face. • When properly used, mineral sunscreens will leave a whitish tint when first applied.

• Reapply: • after 80 minutes of swimming or sweating • immediately afrer towel drying • at least every 2 hours
• Sun Protection Measures. Spending time in the sun increases your risk of skin cancer and early skin aging. To decrease this risk, regularly use a sunscreen with a broad spectrum SPF of 15 or higher and other sun protection measures including: • limit time in the sun, especially from: 10 a.m. -2 p.m. • wear long-sleeve shirts, pants, hats, and sunglasses

• Children under 6 months: Ask a doctor

OTHER SAFETY INFORMATION

- May stain fabrics
- Protect this product from excessive heat and direct sun

INACTIVE INGREDIENT

Water, Helianthus Anuus (Sunflower) Seed Oil, Olea Europaea (Olive) Fruit Oil, Butyloctyl Salicylate, lsocetyl Stearoyl Stearate, Methyl Dihydrobietate, Polysorbate 20, Cetearyl Alcohol, Bentonite, Propanediol, Aloe Barbadensis Leaf Juice, Vitis Vinifera (Grape) Seed Oil, Rubus ldaeus (Raspberry) Seed Oil, Daucus Carota Saliva (Carrot) Seed Oil, Bisabolol, Coco-Glucoside, Microstalline Cellulose, Cellulose Gum, Sodium Gluconate, Sodium Stearoyl Glutamate, Caprylhydroxamic Acid, Polyester-8, Alumina, Silica, Tocopherol, Citric Acid, Caprylic/Capric Triglyceride, Alcohol, Vanillin, Gamma-Nonalactone, Allyl Heptoate, Gamma Octalactone, Heliotropine, Raspberry Ketone, Triethyl Citrate

QUESTIONS

Call 760-940-2125